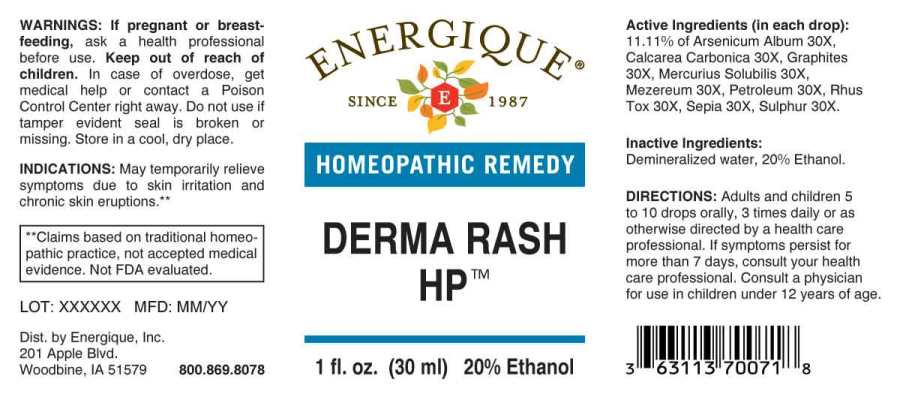 DRUG LABEL: Derma Rash HP
NDC: 44911-0567 | Form: LIQUID
Manufacturer: Energique, Inc.
Category: homeopathic | Type: HUMAN OTC DRUG LABEL
Date: 20240123

ACTIVE INGREDIENTS: ARSENIC TRIOXIDE 30 [hp_X]/1 mL; OYSTER SHELL CALCIUM CARBONATE, CRUDE 30 [hp_X]/1 mL; GRAPHITE 30 [hp_X]/1 mL; MERCURIUS SOLUBILIS 30 [hp_X]/1 mL; DAPHNE MEZEREUM BARK 30 [hp_X]/1 mL; KEROSENE 30 [hp_X]/1 mL; TOXICODENDRON PUBESCENS LEAF 30 [hp_X]/1 mL; SEPIA OFFICINALIS JUICE 30 [hp_X]/1 mL; SULFUR 30 [hp_X]/1 mL
INACTIVE INGREDIENTS: WATER; ALCOHOL

DRUG FACTS:

ACTIVE INGREDIENTS:

(in each drop): 11.11% of Arsenicum Album 30X, Calcarea Carbonica 30X, Graphites 30X, Mercurius Solubilis 30X, Mezereum 30X, Petroleum 30X, Rhus Tox 30X, Sepia 30X, Sulphur 30X.

INDICATIONS:

May temporarily relieve symptoms due to skin irritation and chronic skin eruptions.**

**Claims based on traditional homeopathic practice, not accepted medical evidence. Not FDA evaluated.

WARNINGS:

If pregnant or breastfeeding, ask a health professional before use.

Keep out of reach of children. In case of overdose, get medical help or contact a Poison Control Center right away.

Do not use if tamper evident seal is broken or missing.

Store in a cool, dry place.

KEEP OUT OF REACH OF CHILDREN:

In case of overdose, get medical help or contact a Poison Control Center right away.

DIRECTIONS:

Adults and children 5 to 10 drops orally, 3 times daily or as otherwise directed by a health care professional. If symptoms persist for more than 7 days, consult your health care professional. Consult a physician for use in children under 12 years of age.

INDICATIONS:

May temporarily relieve symptoms due to skin irritation and chronic skin eruptions.**

**Claims based on traditional homeopathic practice, not accepted medical evidence. Not FDA evaluated.

INACTIVE INGREDIENTS:

Demineralized water, 20% Ethanol.

QUESTIONS:

Dist. by Energique, Inc.
201 Apple Blvd.
Woodbine, IA 51579 800.869.8078

PACKAGE LABEL DISPLAY:

ENERGIQUE
SINCE 1987
HOMEOPATHIC REMEDY
DERMA RASH HP
1 fl. oz. (30 ml)